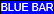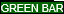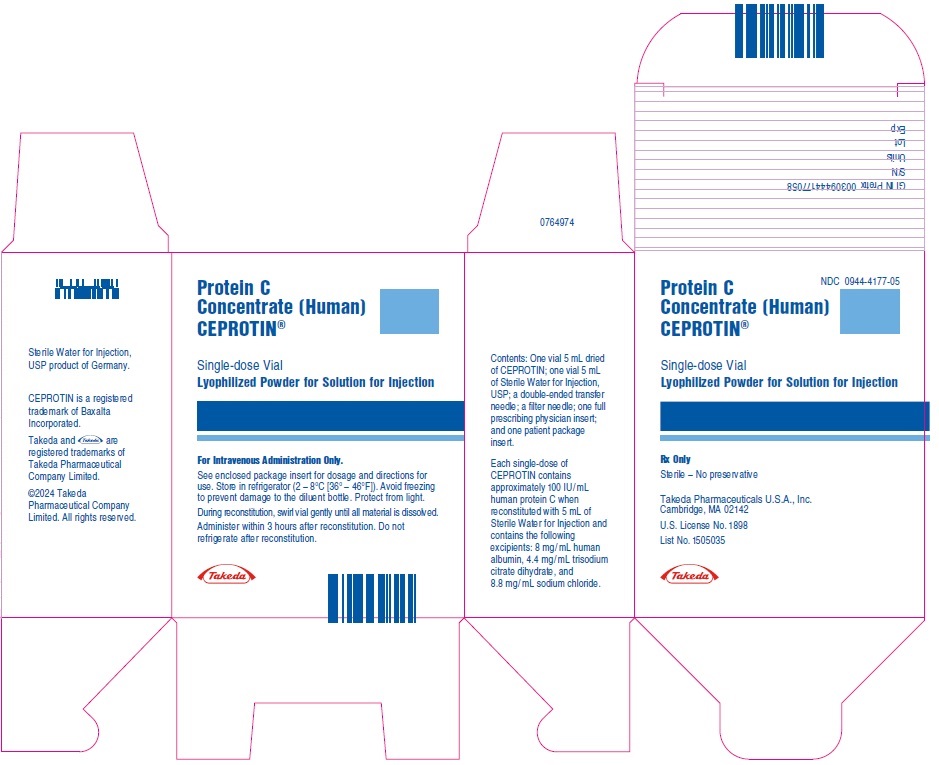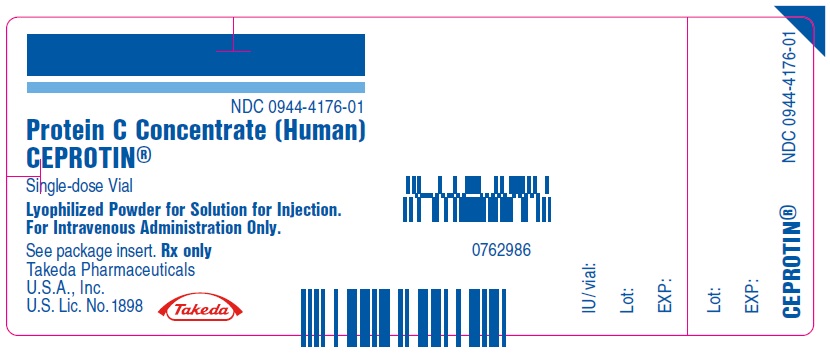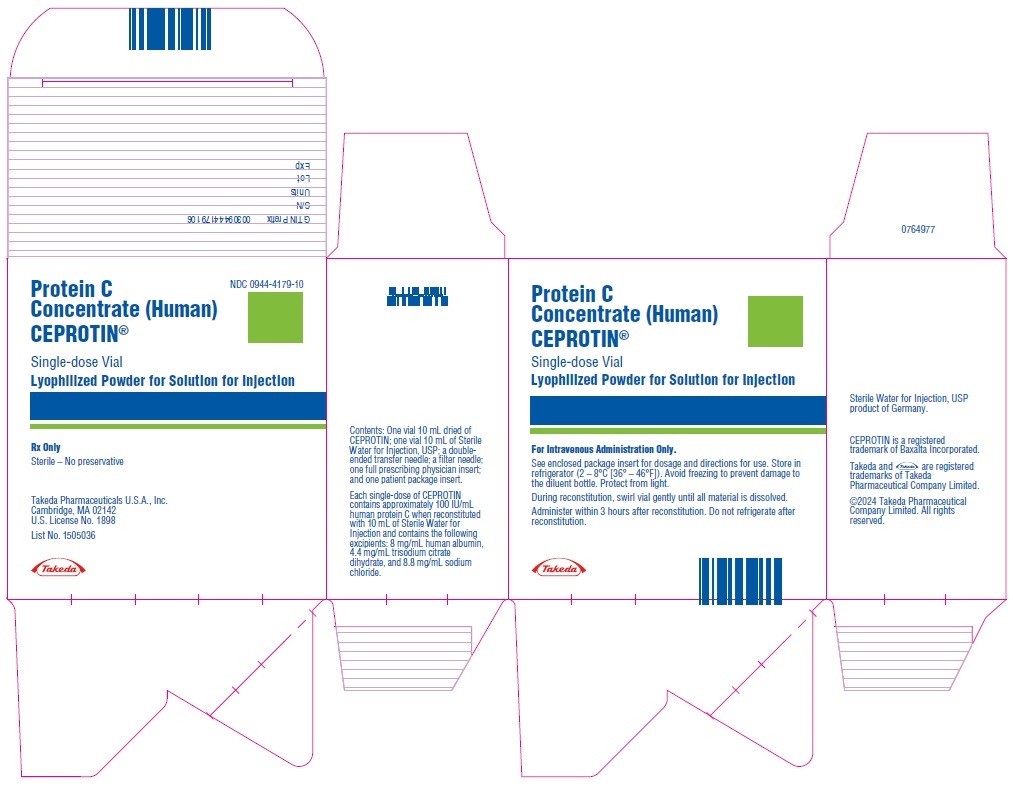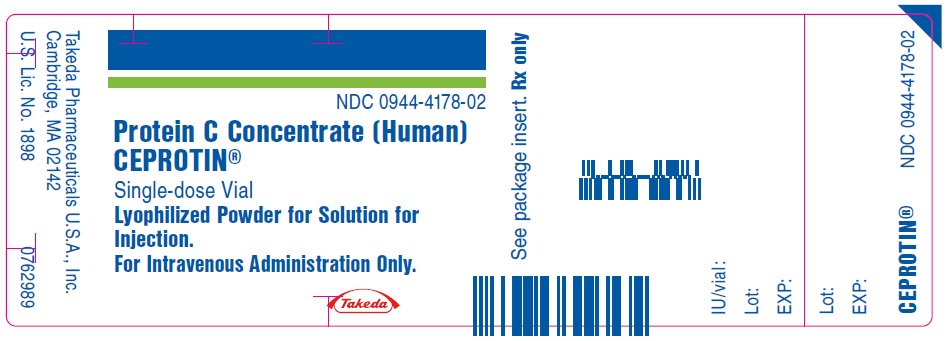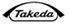 DRUG LABEL: CEPROTIN
NDC: 0944-4177 | Form: KIT | Route: INTRAVENOUS
Manufacturer: Takeda Pharmaceuticals America, Inc.
Category: other | Type: PLASMA DERIVATIVE
Date: 20251204

ACTIVE INGREDIENTS: PROTEIN C 500 [iU]/5 mL
INACTIVE INGREDIENTS: ALBUMIN HUMAN; TRISODIUM CITRATE DIHYDRATE; SODIUM CHLORIDE; WATER 5 mL/5 mL

HIGHLIGHTS OF PRESCRIBING INFORMATION

These highlights do not include all the information needed to use CEPROTIN safely and effectively. See full prescribing information for CEPROTIN.
CEPROTIN® [Protein C Concentrate (Human)] Lyophilized Powder for Solution for Injection
Initial U.S. Approval: 2007

1 INDICATIONS AND USAGE

CEPROTIN, Protein C Concentrate (Human), is an anticoagulant indicated for neonates, pediatric and adult patients with severe congenital Protein C deficiency for the prevention and treatment of venous thrombosis and purpura fulminans. (1)

2 DOSAGE AND ADMINISTRATION

For intravenous administration only.

- Initiate treatment under the supervision of a physician experienced in using coagulation factors/inhibitors where monitoring of Protein C activity is feasible. (2.1)
- Table provides the CEPROTIN dosing schedule for acute episodes, short-term prophylaxis, and long-term prophylaxis*
   | Initial Dose [Adjust the dose according to the pharmacokinetic profile for each individual patient(2.1).] | Subsequent 3 Doses | Maintenance Dose
  Acute Episodes, Short-term Prophylaxis [Continue CEPROTIN until desired anticoagulation is achieved., NA = Not applicable; Q = every.] | 100-120 IU/kg | 60-80 IU/kg Q 6 hours | 45-60 IU/kg Q 6 or Q 12 hours
  Long-term Prophylaxis | NA | NA | 45-60 IU/kg Q 12 hours
  *Dosing is based upon a clinical trial of 15 patients.
- Administer CEPROTIN at a maximum injection rate of 2 mL per minute except for children with a bodyweight of < 10 kg, where the injection rate should not exceed a rate of 0.2 mL/kg/minute.

3 DOSAGE FORMS AND STRENGTHS

: Approximately 500 IU/vial (3)

: Approximately 1000 IU/vial (3)

4 CONTRAINDICATIONS

None. (4)

5 WARNINGS AND PRECAUTIONS

- Discontinue administration of CEPROTIN if symptoms of hypersensitivity/allergic reactions occur. (2.1, 5.1, 6)
- Because CEPROTIN is made from human plasma, it may carry a risk of transmitting infectious agents, e.g., viruses, the variant Creutzfeldt-Jakob disease (vCJD) agent, and theoretically, the Creutzfeldt-Jakob disease agent. (5.2, 11)
- Simultaneous administration of CEPROTIN with tPA and/or anticoagulants may increase the risk of bleeding. (5.3)
- CEPROTIN contains heparin. If heparin-induced thrombocytopenia is suspected, check platelet counts immediately and discontinue administration. (5.4)
- CEPROTIN contains sodium >200 mg. Inform patients on a low sodium diet and/or patients with renal impairment. (5.5)

6 ADVERSE REACTIONS

Common adverse reactions observed in clinical trials were rash, itching, and lightheadedness. (5.1, 6)

To report SUSPECTED ADVERSE REACTIONS, contact Takeda Pharmaceuticals U.S.A., Inc. at 1-877-TAKEDA-7 (1-877-825-3327) or FDA at 1-800-FDA-1088 or www.fda.gov/medwatch.

FULL PRESCRIBING INFORMATION

1 INDICATIONS AND USAGE

CEPROTIN®, Protein C Concentrate (Human), is an anticoagulant indicated for neonates, pediatric and adult patients with severe congenital Protein C deficiency for the prevention and treatment of venous thrombosis and purpura fulminans.

2 DOSAGE AND ADMINISTRATION

For intravenous administration only.

2.1 Dose

- Initiate treatment with CEPROTIN under the supervision of a physician experienced in replacement therapy with coagulation factors/inhibitors where monitoring of protein C activity is feasible.
- The dose, administration frequency, and duration of treatment with CEPROTIN depends on the severity of the protein C deficiency, the patient's age, the clinical condition of the patient, and the patient's plasma level of protein C.
- Adjust the dose regimen according to the pharmacokinetic profile for each individual patient. [See DOSAGE AND ADMINISTRATION: Protein C Activity Monitoring].

Table 1 provides the CEPROTIN dosing schedule for acute episodes, short-term prophylaxis and long-term prophylaxis.

Table 1: CEPROTIN Dosing Schedule for Acute Episodes, Short-term Prophylaxis and Long-term Prophylaxis [Dosing is based upon a clinical trial of 15 patients.]
 | Initial Dose [Adjust the dose according to the pharmacokinetic profile for each individual patient.] | Subsequent 3 Doses | Maintenance Dose
Acute Episode / Short-term Prophylaxis [Continue CEPROTIN until desired anticoagulation is achieved.] | 100-120 IU/kg | 60 - 80 IU/kg Q 6 hours | 45 - 60 IU/kg Q 6 or 12 hours
Long-term Prophylaxis | NA | NA | 45 - 60 IU/kg Q 12 hours
NA = Not applicable; Q = every.

- Determine protein C recovery and half-life with an initial dose of 100-120 IU/kg in patients receiving treatment for acute episodes and short-term prophylaxis.
- Adjust the dose to maintain a target peak protein C activity of 100 %.
- Continue the patient on the same dose after resolution of the acute episode to maintain trough protein C activity level above 25% for the duration of treatment.
- Patients receiving prophylactic administration of CEPROTIN may warrant higher peak protein C activity levels in situations of an increased risk of thrombosis (such as infection, trauma, or surgical intervention). Therefore it is recommended to maintain trough protein C activity levels above 25%.
- These dosing guidelines are also recommended for neonatal and pediatric patients [See USE IN SPECIFIC POPULATIONS: Pediatric Use (8.4) and CLINICAL PHARMACOLOGY: Pharmacokinetics (12.3)].

Protein C Activity Monitoring

- Determine the patient's protein C plasma level before and during treatment with CEPROTIN by measuring protein C activity using a chromogenic assay.Certain clinical conditions, such as acute thrombosis, purpura fulminans, and skin necrosis, may shorten the half-life of CEPROTIN. See CLINICAL PHARMACOLOGY: Pharmacokinetics (12.3). In case of an acute thrombotic event, immediately measure protein C activity before the next injection until the patient is stable and monitor the protein C levels to maintain the trough protein C level above 25%.
- Patients treated during the acute phase of their disease may display much lower increases in protein C activity. In addition to protein C activity measurement, check the coagulation parameters also;however, data were insufficient to establish correlation between protein C activity levels and coagulation parameters in clinical trials.

Initiation of Vitamin K Antagonists

- In patients starting treatment with oral anticoagulants belonging to the class of vitamin K antagonists, a transient hypercoagulable state may arise before the desired anticoagulant effect becomes apparent. This transient effect may be because protein C, a vitamin K-dependent plasma protein, has a shorter half-life than most of the vitamin K-dependent proteins (i.e., Factor II, IX, and X).
- In the initial phase of treatment, the protein C activity is more rapidly suppressed than that of the procoagulant factors. For this reason, if the patient switched to oral anticoagulants, they must continue protein C replacement until stable anticoagulation is obtained. Although warfarin-induced skin necrosis can occur in any patient during the initiation of treatment with oral anticoagulant therapy, individuals with severe congenital protein C deficiency are particularly at risk.
- During the initiation of oral anticoagulant therapy, it is advisable to start with a low dose of the anticoagulant and adjust this incrementally, rather than use a standard loading dose of the anticoagulant.

2.2 Preparation

Reconstitution: Use Aseptic Technique

1. Bring the CEPROTIN (powder) and Sterile Water for Injection, USP (diluent) to room temperature.
2. Remove caps from the CEPROTIN and diluent vials.
3. Cleanse stoppers with germicidal solution, and allow them to dry before use.
4. Remove protective covering from one end of the double-ended transfer needle and insert the exposed needle through the center of the diluent vial stopper.
5. Remove protective covering from the other end of the double-ended transfer needle. Invert diluent vial over the upright CEPROTIN vial; then rapidly insert the free end of the needle through the CEPROTIN vial stopper at its center. The vacuum in the vial will draw in the diluent. If there is no vacuum in the vial, do not use the product, and contact Takeda Pharmaceuticals Customer Service at 1-877-TAKEDA-7 (1-877-825-3327).
6. Disconnect the two vials by removing the needle from the diluent vial stopper. Then, remove the transfer needle from the CEPROTIN vial. Gently swirl the vial until all powder is dissolved. Be sure that CEPROTIN is completely dissolved; otherwise, active materials will be removed by the filter needle.

2.3 Administration

Administration: Use Aseptic Technique

Visually inspect CEPROTIN for particulate matter and discoloration before administration.

After reconstitution, the solution should be colorless to slightly yellowish and clear to slightly opalescent, and free of visible particles. Do not use the solution if it does not meet these criteria. Administer CEPROTIN at room temperature not more than 3 hours after reconstitution.

1. Attach the filter needle to a sterile, disposable syringe and draw back the plunger to admit air into the syringe.
2. Insert the filter needle into the vial of reconstituted CEPROTIN.
3. Inject air into the vial and then withdraw the reconstituted CEPROTIN into the syringe.
4. Remove and discard the filter needle in a hard-walled Sharps container for proper disposal. Use filter needles to filter the contents of a single vial of CEPROTIN only.
5. Attach a suitable needle or infusion set with winged adapter, and inject intravenously as instructed below under Administration by infusion.

Record the name and batch number of the product every time CEPROTIN is administered to a patient.

Administration by Infusion

Administer CEPROTIN at a maximum injection rate of 2 mL per minute except for children with a bodyweight of < 10 kg, where the injection rate should not exceed a rate of 0.2 mL/kg/minute.

3 DOSAGE FORMS AND STRENGTHS

CEPROTIN is available in single-dose vials that contain nominally 500 (blue color bar) or 1000 (green color bar) International Units (IU) human protein C and is reconstituted with 5 mL and 10 mL of Sterile Water for Injection respectively, to provide a single dose of human Protein C at a concentration of 100 IU/mL.

CEPROTIN, when reconstituted with the appropriate volume of diluent, contains the following excipients: 8 mg/mL human albumin, 4.4 mg/mL trisodium citrate dihydrate, and 8.8 mg/mL sodium chloride.

4 CONTRAINDICATIONS

None.

5 WARNINGS AND PRECAUTIONS

5.1 Hypersensitivity

CEPROTIN may contain traces of mouse protein and/or heparin as a result of the manufacturing process. Allergic reactions to mouse protein and/or heparin cannot be ruled out. If symptoms of hypersensitivity/allergic reaction occur, discontinue the injection/infusion. In case of anaphylactic shock, the current medical standards for treatment are to be observed.

5.2 Transmissible Infectious Agents

Because CEPROTIN is made from human plasma, it may carry a risk of transmitting infectious agents, e.g., viruses, the variant Creutzfeldt-Jakob disease (vCJD) agent, and theoretically, the Creutzfeldt-Jakob disease agent.

All infections suspected by a physician to have been possibly transmitted by this product should be reported by the physician or other healthcare provider to Takeda Pharmaceuticals at 1-877-TAKEDA-7 (1-877-825-3327). Discuss the risks and benefits of this product with your patient.

5.3 Bleeding Episodes

Several bleeding episodes have been observed in clinical studies. Concurrent anticoagulant medication may have been responsible for these bleeding episodes. However, it cannot be completely ruled out that the administration of CEPROTIN further contributed to these bleeding events.

Simultaneous administration of CEPROTIN and tissue plasminogen activator (tPA) may further increase the risk of bleeding from tPA.

5.4 Heparin-induced Thrombocytopenia (HIT)

CEPROTIN contains trace amounts of heparin which may lead to Heparin-induced Thrombocytopenia, which can be associated with a rapid decrease of the number of thrombocytes. Identifying HIT is complicated because these symptoms may already be present in acute phase patients with severe congenital protein C deficiency. Determine the platelet count immediately and consider discontinuation of CEPROTIN.

5.5 Low Sodium Diet/Renal Impairment

Inform patients on a low sodium diet that the quantity of sodium in the maximum daily dose of CEPROTIN exceeds 200 mg. Monitor patients with renal impairment closely for sodium overload.

6 ADVERSE REACTIONS

The common adverse reactions related to CEPROTIN treatment observed were the following hypersensitivity or allergic reactions: lightheadedness and itching and rash.

6.1 Clinical Trials Experience

Because clinical trials are conducted under widely varying conditions, adverse reaction rates observed in one clinical trial of a drug cannot be directly compared to rates in the clinical trials of another drug and may not reflect the rates observed in practice.

The safety profile of CEPROTIN was based on 121 patients from clinical studies and compassionate use in severe congenital Protein C deficiency. Duration of exposure ranged from 1 day to 8 years. One patient experienced hypersensitivity/allergic reactions (itching and rash) and lightheadedness which were determined by the investigator to be related to CEPROTIN.

No inhibiting antibodies to CEPROTIN have been observed in clinical studies. However, the potential for developing antibodies cannot be ruled out.

6.2 Postmarketing Experience

The following adverse reactions have been identified during postapproval use of CEPROTIN. Because these reactions are reported voluntarily from a population of uncertain size, it is not always possible to reliably estimate their frequency or establish a causal relationship to drug exposure.

Psychiatric Disorders: Restlessness

Skin and Subcutaneous Tissue Disorders: Hyperhydrosis

General Disorders and Administration Site Conditions: Injection Site Reaction

7 DRUG INTERACTIONS

No formal drug interaction studies have been conducted.

[See WARNINGS AND PRECAUTIONS: Bleeding Episodes (5.3)] for information regarding simultaneous administration of CEPROTIN and tissue plasminogen activator (tPA).

[See DOSAGE AND ADMINISTRATION: Dose (2.1) Initiation of Vitamin K Antagonists].

8 USE IN SPECIFIC POPULATIONS

8.1 Pregnancy

Risk Summary

There are no data with CEPROTIN use in pregnant women to inform a drug-associated risk. Animal reproduction studies have not been conducted with CEPROTIN. It is also not known whether CEPROTIN can cause fetal harm when administered to a pregnant woman or can affect reproduction capacity.

CEPROTIN has not been studied for use during labor and delivery.

In the U.S. general population, the estimated background risk of major birth defects and miscarriages in clinically recognized pregnancies is 2-4% and 15-20%, respectively, regardless of drug exposure.

8.2 Lactation

Risk Summary

There is no information regarding the presence of CEPROTIN in human milk, the effect on the breastfed infant, or the effects on milk production. CEPROTIN has not been studied for use in nursing mothers.

The developmental and health benefits of breastfeeding should be considered along with the mother's clinical need for CEPROTIN and any potential adverse effects on the breastfed child from CEPROTIN or from the underlying maternal condition.

8.4 Pediatric Use

Neonatal and pediatric subjects were enrolled during the prospective and retrospective studies described in CLINICAL STUDIES (14). Of the 18 subjects enrolled during the prospective study, 1 was newborn, 3 were between 28 days and 23 months, 9 were between 2 and 11 years, 1 was between 12 and 16 years, and 4 were older than 16 years. Of the 11 subjects enrolled and treated during the retrospective study, 9 were between 2 and 11 years, and 2 were older than 16 years [see CLINICAL STUDIES (14)].

8.5 Geriatric Use

Clinical studies of CEPROTIN did not include sufficient numbers of subjects aged 65 and over to determine whether they respond differently from younger subjects.

11 DESCRIPTION

CEPROTIN [Protein C Concentrate (Human)] is manufactured from human plasma purified by a combination of filtration and chromatographic procedures, including a column of immobilized mouse monoclonal antibodies on gel beads [See WARNINGS AND PRECAUTIONS: Transmissible Infectious Agents (5.2)].

The manufacturing process for CEPROTIN includes processing steps designed to reduce the risk of viral transmission. The capacity of the manufacturing process to remove and/or inactivate enveloped and non-enveloped viruses has been validated by laboratory spiking studies on a scaled down process model, using the following enveloped and non-enveloped viruses: Human Immunodeficiency Virus Type 1 (HIV-1), Bovine Viral Diarrhea Virus (BVDV), Tick-Borne Encephalitis Virus (TBEV), Pseudorabies Virus (PRV), Hepatitis A Virus (HAV) and Mice Minute Virus (MMV). Virus reduction steps consist of detergent treatment (Polysorbate 80, P80), heat inactivation (Vapor Heating) and immunoaffinity chromatography (IAX).

Virus clearance studies for CEPROTIN have demonstrated that the process provides for a robust overall virus clearance capacity. A summary of log10 virus reduction factors per virus and manufacturing step is presented in Table 2.

Table 2: Summary of Mean Log10 Virus Reduction Factors for the CEPROTIN Manufacturing Process
Manufacturing Step | HIV-1 | HCV Model Viruses |  | PRV | HAV | MMV
Manufacturing Step | HIV-1 | BVDV | TBEV | PRV | HAV | MMV
P80 Treatment | >5.1 | >4.7 | n.d. | 2.5 [Coupled with IEX. I] | >3.8 | 1.4
IAX | 3.9 | 2.9 | 3.8 | 4.0 | 0.9 | 3.5
Vapor Heating | 4.6 | >5.9 | n.d. | 5.9 | >4.2 | 1.2
Abbreviations: IEX, Ion Exchange Chromatography; IAX, Immunoaffinity Chromatography; HIV-1, Human Immunodeficiency Virus Type I; TBEV, Tick-Borne Encephalitis Virus (model for hepatitis C virus [HCV]); BVDV, Bovine Viral Diarrhea Virus (model virus for HCV and other small, enveloped RNA viruses); PRV, Pseudorabies Virus (model virus for enveloped DNA viruses, e.g. HBV, Hepatitis B Virus); HAV, Hepatitis A Virus; MMV, Mice Minute Virus (model for Human Parvovirus B19 and for non enveloped viruses); n.d., not done.

12 CLINICAL PHARMACOLOGY

12.1 Mechanism of Action

Protein C is the precursor of a vitamin K-dependent anticoagulant glycoprotein (serine protease) that is synthesized in the liver [See DOSAGE AND ADMINISTRATION: Dose (2.1) Initiation of Vitamin K Antagonists]. It is converted by the thrombin/thrombomodulin-complex on the endothelial cell surface to activated Protein C (APC). APC is a serine protease with potent anticoagulant effects, especially in the presence of its cofactor protein S. APC exerts its effect by the inactivation of the activated forms of factors V and VIII, which leads to a decrease in thrombin formation. APC has also been shown to have profibrinolytic effects.

The Protein C pathway provides a natural mechanism for control of the coagulation system and prevention of excessive procoagulant responses to activating stimuli. A complete absence of protein C is not compatible with life. A severe deficiency of this anticoagulant protein causes a defect in the control mechanism and leads to unchecked coagulation activation, resulting in thrombin generation and intravascular clot formation with thrombosis.

12.2 Pharmacodynamics

In clinical studies, the intravenous administration of CEPROTIN demonstrated a temporary increase, within approximately half an hour of administration, in plasma levels of APC. Replacement of protein C in protein C-deficient patients is expected to control or, if given prophylactically, to prevent thrombotic complications.

12.3 Pharmacokinetics

Table 3 provides pharmacokinetic results for asymptomatic and symptomatic subjects with protein C deficiency.

Table 3: Pharmacokinetics of CEPROTIN in Subjects with Severe Congenital Protein C Deficiency
PK parameter | N | Median | 95% CI for median | Min | Max
Cmax [IU/dL] | 21 | 110 | 106 to 127 | 40 | 141
Tmax [h] | 21 | 0.50 | 0.50 to 1.05 | 0.17 | 1.33
Incremental recovery [(IU/dL)/(IU/kg)] | 21 | 1.42 | 1.32 to 1.59 | 0.50 | 1.76
Initial half-life [h] | 21 | 7.8 | 5.4 to 9.3 | 3.0 | 36.1
Terminal half-life [h] | 21 | 9.9 | 7.0 to 12.4 | 4.4 | 15.8
Half-life by the non-compartmental approach [h] | 21 | 9.8 | 7.1 to 11.6 | 4.9 | 14.7
AUC0-Infinity [IU*h/dL] | 21 | 1500 | 1289 to 1897 | 344 | 2437
MRT [h] | 21 | 14.1 | 10.3 to 16.7 | 7.1 | 21.3
Clearance [dL/kg/h] | 21 | 0.0533 | 0.0428 to 0.0792 | 0.0328 | 0.2324
Volume of distribution at steady state [dL/kg] | 21 | 0.74 | 0.70 to 0.89 | 0.44 | 1.65
Cmax = Maximum concentration after infusion; T max = Time at maximum concentration; AUC 0-Infinity = Area under the curve from 0 to infinity; MRT = Mean residence time; and Incremental recovery = Maximum increase in Protein C concentration following infusion divided by dose

The protein C plasma activity was measured by chromogenic and/or clotting assay. The maximum plasma concentrations (Cmax) and area under the plasma concentration-time curve (AUC) appeared to increase dose-linearly between 40 and 80 IU/kg. The median incremental recovery was 1.42 [(IU/dL)/(IU/kg)] after intravenous administration of CEPROTIN. The median half-lives, based on non-compartmental method, ranged from 4.9 to 14.7 hours, with a median of 9.8 hours. In patients with acute thrombosis, both the increase in protein C plasma levels as well as half-life may be considerably reduced. No formal study or analysis has been performed to evaluate the effect of covariates such as race and gender on the pharmacokinetics of CEPROTIN.

The pharmacokinetic profile in pediatric patients has not been formally assessed. Limited data suggest that the pharmacokinetics of CEPROTIN may be different between very young children and adults. The systemic exposure (Cmax and AUC) may be considerably reduced due to a faster clearance, a larger volume of distribution, and/or a shorter half-life of protein C in very young children than in older subjects. Consider this fact when a dosing regimen for children is determined. Doses should be individualized based upon protein C activity levels [See DOSAGE AND ADMINISTRATION: Dose (2.1) Protein C Activity Monitoring].

13 NONCLINICAL TOXICOLOGY

13.1 Carcinogenesis, Mutagenesis, Impairment of Fertility

Protein C contained in CEPROTIN is a normal constituent of human plasma and acts like endogenous protein C. Studies in heterologous species to evaluate carcinogenicity, reproductive toxicology and developmental toxicology have not been performed.

CEPROTIN has not demonstrated mutagenic potential in the Salmonella Thyphimurium reverse mutation assay (Ames test).

13.2 Animal Toxicology and/or Pharmacology

Safety Pharmacology:

Cardio-respiratory studies performed in dogs evaluating mean arterial pressure, cardiac output, systemic vascular resistance, heart rate, QT interval changes, pulmonary artery pressure, respiratory rate and respiratory minute volume demonstrated no adverse effects at a maximum dose of 500 IU/kg. Anaphylactoid reactions as determined by measurement of bronchospastic activity in guinea pigs demonstrated no adverse effects at the maximum dose of 300 IU/kg. Thrombogenic potential was evaluated in rabbits using the Wessler stasis model and demonstrated no adverse effects at 200 IU/kg. Overall, safety pharmacology studies evaluating cardio-respiratory function, acute dose anaphylactoid potential and thrombogenicity demonstrated no adverse effects in a range of doses from 1.6 to 4.2 times the maximum single human dosage per kilogram body weight.

Acute Dose Toxicity:

Toxicity testing in rats and mice following single dosing of 2000 IU/kg or 1500 IU/kg, respectively, demonstrated no adverse clinical effects or gross pathology at 14 days post dosing.

Repeated Dose Toxicity:

Studies were not conducted to evaluate repeated-dose toxicity in animals. Prior experience with CEPROTIN has suggested immunogenic response in heterologous species following repeated dosing of this human derived protein. Thus, the long-term toxicity potential of CEPROTIN following repeated dosing in animals is unknown.

Local Tolerance Testing:

Investigation of route of injection tolerance demonstrated that CEPROTIN did not result in any local reactions after intravenous, intra-arterial injections of 500 IU/kg (5 mL) and paravenous injections of 100 IU/kg (1 mL) in rabbits.

Citrate Toxicity:

CEPROTIN contains 4.4 mg of Trisodium Citrate Dihydrate (TCD) per mL of reconstituted product. Studies in mice evaluating 1000 IU vials reconstituted with 10 mL vehicle followed by dosing at 30 mL/kg (132 mg/kg TCD) and 60 mL/kg (264 mg/kg TCD) resulted in signs of citrate toxicity (dyspnea, slowed movement, hemoperitoneum, lung and thymus hemorrhage and renal pelvis dilation).

14 CLINICAL STUDIES

In a multi-center, open-label, non-randomized study in 3 parts, the safety and efficacy of CEPROTIN was evaluated in subjects with severe congenital protein C deficiency for the (on-demand) treatment of acute thrombotic episodes, such as purpura fulminans (PF), warfarin-induced skin necrosis (WISN) and other thromboembolic events, and for short-term or long-term prophylaxis. Eighteen subjects (9 male and 9 female), ages ranging from 0 (newborn) to 25.7 years participated in this study.

The clinical endpoint of the study was to assess whether episodes of PF and/or other thromboembolic events were treated effectively, effectively with complications, or not treated effectively. Table 4 provides a comparison of the primary efficacy ratings of PF from the study to the historical controls. Inadequate data is available for treatment of WISN.

Table 4: Comparison of Primary Efficacy Ratings of Episodes of Purpura Fulminans in the Protein C Concentrate (Human) Study of Historical Controls
 |  | Protein C Concentrate (Human) |  | Historical Controls
Episode Type | Primary Efficacy Rating | N | % | N | %
Purpura Fulminans | Effective | 17 | 94.4 | 11 | 52.4
Purpura Fulminans | Effective with Complication | 1 | 5.6 | 7 | 33.3
Purpura Fulminans | Not Effective | 0 | 0.0 | 3 | 14.3
Purpura Fulminans | Total | 18 | 100 | 21 | 100

Of 18 episodes of PF (6 severe, 11 moderate, 1 mild) treated with CEPROTIN for the primary efficacy rating, 17 (94.4%) were rated as effective, and 1 (5.6%) was rated as effective with complications; none (0%) were rated not effective. When compared with the efficacy ratings for 21 episodes of PF (historical control group), subjects with severe congenital protein C deficiency were more effectively treated with CEPROTIN than those treated with modalities such as fresh frozen plasma or conventional anticoagulants.

Table 5 provides a summary of the secondary treatment ratings for treatment of skin lesions and other thrombotic episodes from part one of the study.

Table 5: Summary of Secondary Treatment Ratings for Treatment of Skin Lesions and Other Thrombotic Episodes - Protein C Concentrate (Human) Study Part 1
 | Purpura Fulminans Skin Necrosis |  |  |  |  |  |  |  | Other Thrombotic Events |  | Total
 | Mild |  | Moderate |  | Severe |  | Total |  | Total
Rating Category | N | % | N | % | N | % | N | % | N | % | N | %
Excellent | 1 | 5.6 | 7 | 38.9 | 5 | 27.8 | 13 | 72.2 | 4 | 80.0 | 17 | 73.9
Good | 0 | 0.0 | 4 | 22.2 | 0 | 0.0 | 4 | 22.2 | 1 | 20.0 | 5 | 21.7
Fair | 0 | 0.0 | 0 | 0.0 | 1 | 5.6 | 1 | 5.6 | 0 | 0 | 1 | 4.3
Total | 1 | 5.6 | 11 | 61.1 | 6 | 33.3 | 18 | 100.0 | 5 | 100.0 | 23 | 100.0
N = Number of episodes

In a secondary efficacy rating, 13 (72.2%) of the 18 episodes of PF treated with CEPROTIN were rated as excellent, 4 (22.2%) were rated as good, and 1 (5.6%) episode of severe PF was rated as fair; all were rated as effective. Four (80%) of the 5 episodes of venous thrombosis had treatment ratings of excellent, while 1 (20%) was rated as good.

CEPROTIN was also demonstrated to be effective in reducing the size and number of skin lesions. Non-necrotic skin lesions healed over a maximum 12-day (median 4-day) period and necrotic skin lesions healed over a maximum 52-day (median 11-day) period of CEPROTIN treatment, as shown in Table 6.

Table 6: Number of Days to Complete Healing of Skin Lesions in the Protein C Concentrate (Human) Study
Lesion Type | Number of Episodes (Number of Subjects) | Mean | Median | Minimum | Maximum
Non-necrotic | 16 (9 subjects) | 4.6 | 4.0 | 1 | 12
Necrotic | 7 (5 subjects) | 21.1 | 11.0 | 5 | 52

Changes in the extent of venous thrombus were also measured for the 5 thromboembolic episodes. CEPROTIN prevented an increase in the extent of thrombus during 4 (80%) of the thromboembolic episodes by Day 3 of treatment, and 1 (20%) episode by Day 5 of treatment.

All seven of the short-term prophylaxis treatments with CEPROTIN were free of complications of PF or thromboembolic events, as shown in Table 7.

Table 7: Summary of Complications During Short Term Prophylaxis in the Protein C Concentrate (Human) Study
Reason for Treatment | Number of Treatments | Presentation of Purpura Fulminans During Treatment Episodes |  | Thromboembolic Complications During Treatment Episode |  | Number of Treatments Free of Complications
Reason for Treatment | Number of Treatments | N | % | N | % | N | %
Anticoagulation Therapy | 3 | 0 | 0.0 | 0 | 0.0 | 3 | 100.0
Surgical Procedure | 4 | 0 | 0.0 | 0 | 0.0 | 4 | 100.0
Total | 7 | 0 | 0.0 | 0 | 0.0 | 7 | 100.0

No episodes of PF occurred in four subjects ranging from 42 to 338 days of long-term prophylactic treatment with CEPROTIN, as shown in Table 8. When not on prophylactic treatment and receiving CEPROTIN on-demand, the same four subjects experienced a total of 13 (median of 3) episodes of PF over a range of 19 to 323 days. The time to first episode of PF after exiting from long-term prophylaxis treatment ranged from 12 to 32 days for these four subjects.

Table 8: Number and Rate of Episodes of Skin Lesions or Thrombosis for Four Subjects Who Received Long-Term Prophylactic Treatment and Were Treated On-Demand in the Protein C Concentrate (Human) Study
Summary Statistic | Long-Term Prophylactic Treatment |  |  | While On-Demand [Total number of episodes while subjects were On-Demand was 13] |  |  | Time to First Episode After Existing Long Term Prophylaxis
Summary Statistic | Number of Episodes per Subject | Number of Days Receiving Prophylactic Treatment | Monthly Rate of Episodes | Number of Episodes per Subject | Number of Days Not Receiving Study Drug | Monthly Rate of Episodes | Time to First Episode After Existing Long Term Prophylaxis
Mean | 0 | 229 | 0.0 | 3.3 | 165 | 1.91 | Time to First Episode After Existing Long Term Prophylaxis | 23.3
Median | 0 | 268 | 0.0 | 3.0 | 159 | 0.49 | 24.5
Minimum | 0 | 42 | 0.0 | 1.0 | 19 | 0.25 | 12.0
Maximum | 0 | 338 | 0.0 | 6.0 | 323 | 6.40 | 32.0

Retrospective Analysis

A retrospective study to capture dosing information and treatment outcome data in subjects with severe congenital protein C deficiency who were treated with CEPROTIN under an emergency use IND was also conducted. Eleven subjects (6 male and 5 female), ages ranging from 2.1 to 23.8 years participated in this study.

There were 28 acute episodes of PF/WISN and vascular thrombus reported in which time to resolution ranged from 0 to 46 days. The treatment outcome for these episodes was rated effective in all cases except one.

16 HOW SUPPLIED/STORAGE AND HANDLING

CEPROTIN, Protein C Concentrate (Human), is supplied as a sterile, white or cream colored, lyophilized powder for IV injection. It has a pH between 6.7 and 7.3 and an osmolality not lower than 240 mosmol/kg. One International Unit (IU) of protein C corresponds to the amidolytically measured activity of protein C in 1 mL of normal plasma. The potency (IU) is determined using a chromogenic substrate method referenced against the World Health Organization (WHO) International Standard (86/622).

CEPROTIN is available in single-dose vials that contain the following nominal product strengths:

: 500 IU per vial: (NDC: 0944-4177-05)
: 1000 IU per vial: (NDC: 0944-4179-10)

Actual potency is printed on the vial label.

One package of CEPROTIN contains one glass vial of CEPROTIN powder, one glass vial of Sterile Water for Injection, USP, one transfer needle, one filter needle, one full prescribing physician insert and one patient package insert.

STORAGE AND HANDLING

CEPROTIN, packaged for sale, is stable for 3 years when stored refrigerated at 2°C–8°C (36°F-46°F). Do not freeze in order to prevent damage to the diluent vial. Store the vial in the original carton to protect it from light. The reconstituted solution should be used within 3 hours of reconstitution. Do not use beyond the expiration date on the CEPROTIN vial.

17 PATIENT COUNSELING INFORMATION

Advise the patient to read the FDA-approved patient labeling (Patient Information and Instructions for Use).

Inform patients of the following:

- Early signs of hypersensitivity reactions include hives, generalized urticaria, tightness of the chest, wheezing, hypotension and anaphylaxis. The risk of an allergic type hypersensitivity reaction cannot be excluded [See WARNING AND PRECAUTIONS: Hypersensitivity (5.1)]. CEPROTIN may contain traces of mouse protein or heparin as a result of the manufacturing process. Allergic reactions to mouse protein or heparin cannot be ruled out. Immediately discontinue the injection/infusion and inform their physician as soon as possible if symptoms of hypersensitivity/allergic reaction occur.

Takeda Pharmaceuticals U.S.A., Inc.
Cambridge, MA 02142
US License No. 1898

CEPROTIN is a registered trademark of Baxalta Incorporated.
Takeda and are registered trademarks of Takeda Pharmaceutical Company Limited.

©2024 Takeda Pharmaceutical Company Limited. All rights reserved.

CEP367

PATIENT INFORMATION

CEPROTIN® [Protein C Concentrate (Human)]
Pronounced: see PRO ten

Please read this leaflet carefully before using CEPROTIN [Protein C Concentrate (Human)]. This leaflet is based on the information provided to your doctor and is a summary of the important information you need to know about your medicine for your severe congenital Protein C deficiency. This leaflet does not take the place of talking with your doctor and does not contain all of the information available about CEPROTIN.

Use this leaflet only after you have received instructions from your doctor. If you have any questions after reading this leaflet, ask your doctor or pharmacist.

1. What is CEPROTIN and what is it used for?

The name of your medicine is CEPROTIN, pronounced "see PRO ten".

CEPROTIN contains Protein C, a natural protein that is made in the liver and is present in your blood. Protein C is a part of human plasma that regulates the blood clotting (coagulation) system and prevents abnormal clot formation (thrombosis). Plasma is the liquid part of human blood.

CEPROTIN is used to treat patients with Severe Congenital Protein C Deficiency for the prevention and treatment of:

- venous thrombosis (blood clot in the vein), and
- purpura fulminans (blood spots, bruising, and discoloring to skin as a result of clotting of small blood vessels in the skin).

2. How does CEPROTIN work?

CEPROTIN temporarily raises the levels of Protein C in the body. Protein C plays a major role in preventing your body from forming too many blood clots. CEPROTIN is for those patients who either don't produce enough Protein C or whose Protein C doesn't work correctly. CEPROTIN allows your body's blood clotting process to function properly.

3. Who should not use CEPROTIN?

Do not use CEPROTIN unless your doctor confirms that you have severe congenital Protein C deficiency.

Tell your doctor about all your medical conditions.

Allergic to Mouse Protein or Heparin:

If you are known to have allergic-type reactions (rash, hives, itching, tightness of the chest, difficulty breathing, throat tightness, and low blood pressure) to mouse protein or heparin, talk to your doctor before using this product. CEPROTIN contains small amounts of heparin and/or mouse protein as a result of the manufacturing process.

Low Sodium Diet/Kidney Impairment:

Talk with your doctor before using CEPROTIN if you are on a low sodium diet or have problems with your kidney, as the amount of sodium in the maximum daily dose of CEPROTIN exceeds 200 mg.

Pregnancy or Breastfeeding:

Inform your doctor if you are pregnant or breastfeeding. Your doctor will decide if CEPROTIN may be used during pregnancy and/or breastfeeding.

Tell your doctor about all the medicines you are taking, including prescription and nonprescription medicines, vitamins, and herbal supplements. Tell your doctor if you are on a special diet.

4. What is the most important information I need to know about CEPROTIN?

You could have an allergic reaction to CEPROTIN. You should be aware of the early signs of allergic reactions. These include rash, hives, itching, tightness of the chest, difficulty breathing, throat tightness, and low blood pressure. The signs and symptoms of low blood pressure can include a weak pulse, feeling lightheaded or dizzy when you stand, and possibly shortness of breath. If you experience any of these symptoms while being treated with CEPROTIN, stop the treatment and contact your doctor. If you experience a severe allergic reaction, including difficulty breathing and (near) fainting, seek emergency treatment.

You could get an infectious disease since this drug product is made from human plasma. However, there are steps in collecting the plasma and in the making of CEPROTIN to lessen this possibility. For example, blood and plasma donors are screened for certain viral infections. There are also steps in the processing of the plasma that can inactivate or remove viruses.

5. What are the possible side effects of CEPROTIN?

Like all medicines, CEPROTIN can cause side effects, although not everyone gets them.

The common side effects to CEPROTIN observed in clinical trials were hypersensitivity or allergic reactions: lightheadedness itching, and rash.

There have also been individual reports, after the drug was marketed, of restlessness, increased sweating, and injection site reaction.

If you develop any side effects, including any not listed in this leaflet, please contact your doctor.

6. How do I use CEPROTIN?

CEPROTIN is given by intravenous administration (infusion into a vein). It is given to you under the close supervision of your doctor who is experienced in replacement therapy of coagulation factors/inhibitors and where monitoring of protein C activity is possible. Your dosage will vary depending upon your condition, your age, and your body weight. Your doctor may require that you have blood taken to help determine the dose of CEPROTIN that you should get. See the following Instructions for Use.

7. How do I store CEPROTIN?

Store CEPROTIN in powder form, without the diluent (Sterile Water for Injection) added. Store CEPROTIN in the refrigerator at 2°C to 8°C (36°F to 46°F). Store the vial in the original carton to protect it from light. Do not freeze to prevent damage to the diluent vial.

Do not use CEPROTIN beyond the expiration date printed on the CEPROTIN vial.

8. What are the ingredients in CEPROTIN?

Active ingredient: human Protein C

Other ingredients: human albumin, sodium chloride and trisodium citrate dihydrate

9. What does CEPROTIN look like?

CEPROTIN is a white or cream colored powder that is mixed with the water provided in the package (Sterile Water for Injection) before injection. After mixing with the Sterile Water for Injection, the solution is colorless to slightly yellowish and clear to slightly opalescent and free from visible particles.

10. What are the contents of the CEPROTIN package?

CEPROTIN comes in the following strengths:

: Approximate dosage strength of 500 IU per vial.
: Approximate dosage strength of 1000 IU per vial.

One package of CEPROTIN contains one vial of CEPROTIN powder, one vial of Sterile Water for Injection (diluent), one double-ended transfer needle, one filter needle, one full prescribing physician insert, and one patient package insert.

11. How can I contact Takeda for more product information?

Takeda Customer Service: 1-877-TAKEDA-7 (1-877-825-3327)
Product website: www.ceprotin.com

CEP367

Revised: 9/2024

INSTRUCTIONS FOR USE

CEPROTIN® [see-PRO-ten]
Protein C Concentrate (Human)
for intravenous use

This "Instructions for Use" contains information on how to inject CEPROTIN.

IMPORTANT: Contact your doctor if you experience any problems with this procedure. These instructions are intended only as an aid for those patients who have been instructed by their doctor on the proper way to self-infuse the product. Do not attempt to self-infuse unless you have been taught how by your doctor.

1. Prepare a clean surface and gather all the materials you will need for the infusion. You will need to gather exam gloves (optional), alcohol swabs (or other suitable solution suggested by your doctor), a winged infusion set, and a tourniquet, as these are not provided with your package of CEPROTIN.
2. Check the expiration date on the CEPROTIN vial. Do not use CEPROTIN after the expiration date.
3. Let the vial of CEPROTIN and the vial of Sterile Water for Injection, USP (diluent) warm up to room temperature.
4. Wash your hands and put on clean exam gloves (optional).
5. Remove caps from the CEPROTIN and diluent vial to expose the centers of the rubber stoppers.
6. Cleanse the stoppers with an alcohol swab (or other suitable solution suggested by your doctor) by rubbing the stoppers firmly for several seconds and allow them to dry.
7. Remove the protective covering from one end of the double-ended transfer needle and insert the exposed needle through the center of the diluent vial stopper.
8. While keeping the needle in the diluent vial, remove the protective covering from the other end of the double-ended transfer needle.
9. Invert the diluent vial over the upright CEPROTIN vial. Then, insert the free end of the needle through the CEPROTIN vial stopper at its center. The vacuum in the vial will draw in the diluent. If there is no vacuum in the CEPROTIN vial, do not use the product. Contact Takeda Pharmaceuticals Customer Service.
10. Separate the two vials by removing the needle from the diluent vial stopper. Then, remove the transfer needle from the CEPROTIN vial. Do not attempt to recap the needle and do not dispose it in ordinary household trash. Place the needle in a hard-walled Sharps container for proper disposal.
11. Gently swirl the CEPROTIN vial until all the powder is completely dissolved. The solution should be colorless to slightly yellowish and free of visible particles. Do not use the solution if you see particles in it. Administer CEPROTIN at room temperature within 3 hours of mixing.
12. Attach the filter needle to a disposable syringe and draw back the plunger to allow air into the syringe. Insert the filter needle into the reconstituted CEPROTIN.
13. Inject air into the vial, and then withdraw the solution into the syringe.
14. Remove and discard the filter needle from the syringe. Do not attempt to recap the needle and do not dispose it in ordinary household trash. Place the needle in a hard-walled Sharps container for proper disposal.
15. Attach a winged infusion set, if available, or a suitable needle (not supplied) for the injection.
16. Point the needle up and remove any air bubbles by gently tapping the syringe with your finger and slowly and carefully pushing air out of the syringe.
17. Apply a tourniquet, and prepare the injection site by wiping the skin well with an alcohol swab (or other suitable solution suggested by your doctor).
18. Insert the needle into the vein, and remove the tourniquet. Infuse CEPROTIN. CEPROTIN should be administered at a maximum injection rate of 2 milliliters (mL) per minute except for children with a bodyweight of < 10 kg (22 pounds), where the injection rate should not exceed a rate of 0.2 mL per kilogram per minute.
19. Remove the needle from the vein and apply pressure with sterile gauze to the infusion site for several minutes. Do not attempt to recap the needle after the infusion, and do not dispose it in ordinary household trash. Place the needle with the used syringe in a hard-walled Sharps container for proper disposal.
20. Clean up any blood with a freshly prepared mixture of 1 part bleach and 9 parts water, soap, and water, or any household disinfecting solution.

Takeda Pharmaceuticals U.S.A., Inc.
Cambridge, MA 02142
U.S. License No. 1898

CEPROTIN is a registered trademark of Baxalta Incorporated.
Takeda and are registered trademarks of Takeda Pharmaceutical Company Limited.

©2024 Takeda Pharmaceutical Company Limited. All rights reserved.

CEP367

Revised: 9/2024

Important: Contact your doctor if you have any questions or experience any adverse effects. These instructions are intended as an additional aid only for those patients who have been instructed by their doctor on the proper way to self-infuse CEPROTIN. If you have not been instructed to self-infuse by your doctor, do not attempt to self-infuse.

PRINCIPAL DISPLAY PANEL - Kit Carton - NDC 0944-4177-05

NDC 0944-4177-05

Protein C
Concentrate (Human)
CEPROTIN®

Single-dose Vial

Lyophilized Powder for Solution for Injection

For Intravenous Administration Only.

See enclosed package insert for dosage and directions for
use. Store in refrigerator (2 – 8°C [36° – 46°F]). Avoid freezing
to prevent damage to the diluent bottle. Protect from light.

During reconstitution, swirl vial gently until all material is dissolved.

Administer within 3 hours after reconstitution. Do not
refrigerate after reconstitution.

Takeda

PRINCIPAL DISPLAY PANEL - Vial Label - NDC 0944-4176-01

NDC 0944-4176-01

Protein C Concentrate (Human)
CEPROTIN®

Single-dose Vial

Lyophilized Powder for Solution for Injection.
For Intravenous Administration Only.

See package insert. Rx only
Takeda Pharmaceuticals
U.S.A., Inc.
U.S. Lic. No. 1898

Takeda

0762986

PRINCIPAL DISPLAY PANEL - Kit Carton - NDC 0944-4179-10

NDC 0944-4179-10

Protein C
Concentrate (Human)
CEPROTIN®

Single-dose Vial

Lyophilized Powder for Solution for Injection

For Intravenous Administration Only.

See enclosed package insert for dosage and directions for use. Store in
refrigerator (2 – 8°C [36° – 46°F]). Avoid freezing to prevent damage to
the diluent bottle. Protect from light.

During reconstitution, swirl vial gently until all material is dissolved.

Administer within 3 hours after reconstitution. Do not refrigerate after
reconstitution.

Takeda

PRINCIPAL DISPLAY PANEL - Vial Label - NDC 0944-4178-02

NDC 0944-4178-02

Protein C Concentrate (Human)
CEPROTIN®

Single-dose Vial

Lyophilized Powder for Solution for
Injection.
For Intravenous Administration Only.

Takeda